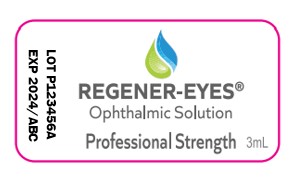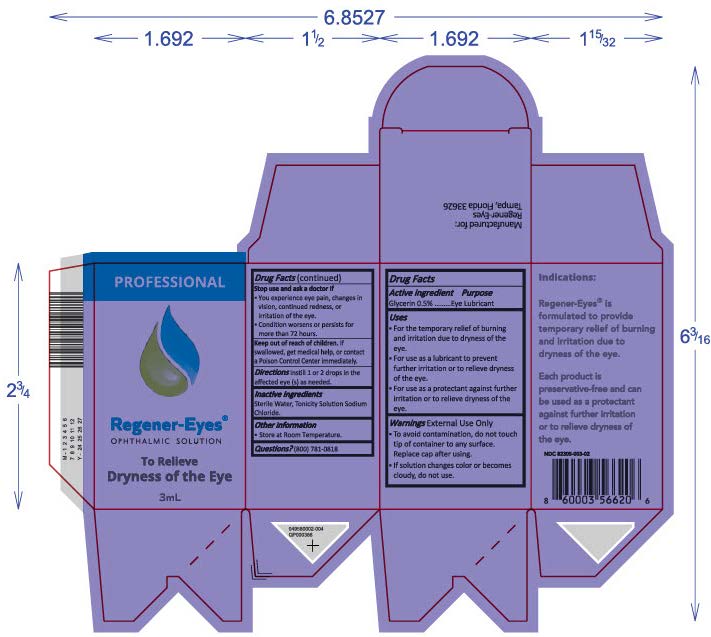 DRUG LABEL: Regener-Eyes
NDC: 82305-003 | Form: SOLUTION/ DROPS
Manufacturer: Regenerative Processing Plant, LLC
Category: otc | Type: HUMAN OTC DRUG LABEL
Date: 20250320

ACTIVE INGREDIENTS: GLYCERIN 15 mg/3 mL
INACTIVE INGREDIENTS: SODIUM CHLORIDE; WATER 15 mg/3 mL

Active Ingredient

Glycerin, 0.5%

Purpose

Eye Lubricant

Uses

- For the temporary relief of burning and irritation due to dryness of the eye.
- For use as a lubricant to prevent further irritation or to relieve dryness of the eye
- For use as a protectant against further irritation or to relieve dryness of the eye.

Warnings

External Use Only

- To avoid contamination, do not touch tip of container to any surface. Replace cap after using.
- If solution changes color or becomes cloudy, do not use.

Stop use and ask a doctor If

- You experience eye pain, changes in vision, continued redness, or irritation of the eye.
- Condition worsens or persists for more than 72 hours.

Keep out of reach of children. If swallowed, get medical help, or contact a Poison Control Center immediately.

Directions

Instill 1 or 2 drops in the affected eye(s) as needed.

RECENT MAJOR CHANGES

Instill 1 or 2 drops in the affected eye(s) as needed.

Inactive Ingredients

Sterile Water, Tonicity Solution Sodium Chloride

Other information

- Store at refrigerated conditions once the bottle closure is activated to the open position.

Questions?

Questions? (800) 781-0818